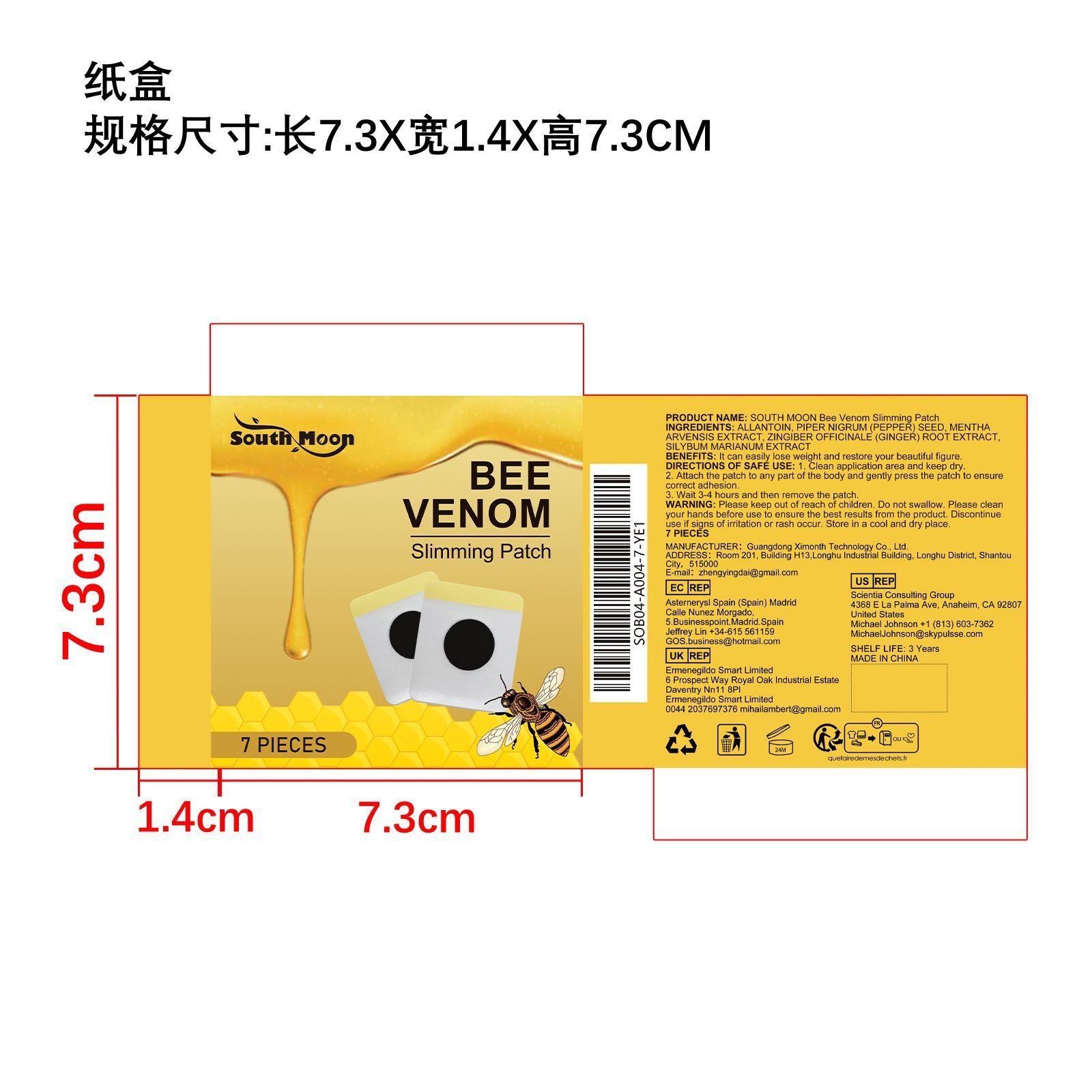 DRUG LABEL: SOUTH MOON Bee Venom Slimming Patch
NDC: 84660-022 | Form: PATCH
Manufacturer: Guangdong Ximonth Technology Co., Ltd.
Category: otc | Type: HUMAN OTC DRUG LABEL
Date: 20240924

ACTIVE INGREDIENTS: MENTHA ARVENSIS WHOLE 2.44 g/12.2 g; WHITE PEPPER 3.05 g/12.2 g; GINGER 1.83 g/12.2 g; MILK THISTLE 1.22 g/12.2 g
INACTIVE INGREDIENTS: ALLANTOIN 3.66 g/12.2 g

Active Ingredient(s)

PIPER NIGRUM (PEPPER) SEED、MENTHA ARVENSIS EXTRACT、ZINGIBER OFFICINALE (GINGER) ROOT EXTRACT、SILYBUM MARIANUM EXTRACT

Purpose

It can easily lose weight and restore your beautiful figure.

Use

1. Clean application area and keep dry.
2. Attach the patch to any part of the body and gently press the patch to ensure correct adhesion.
3. Wait 3-4 hours and then remove the patch.

Warnings

Please keep out of reach of children.Do not swallow.Please clean your hands before use to ensure the best results from the product.Discontinue use if signs of irritation or rash occur.Store in a cool and dry place

Do not use

Discontinue use if signs of irritation or rash occur

STOP USE

Discontinue use if signs of irritation or rash occur.

KEEP OUT OF REACH OF CHILDREN

Please keep out of reach of children. Do not swallow.

STORAGE AND HANDLING

Avoid freezing and excessive heat above 40C (104F) ）
Store in a cool and dry place.

INACTIVE INGREDIENT

ALLANTOIN